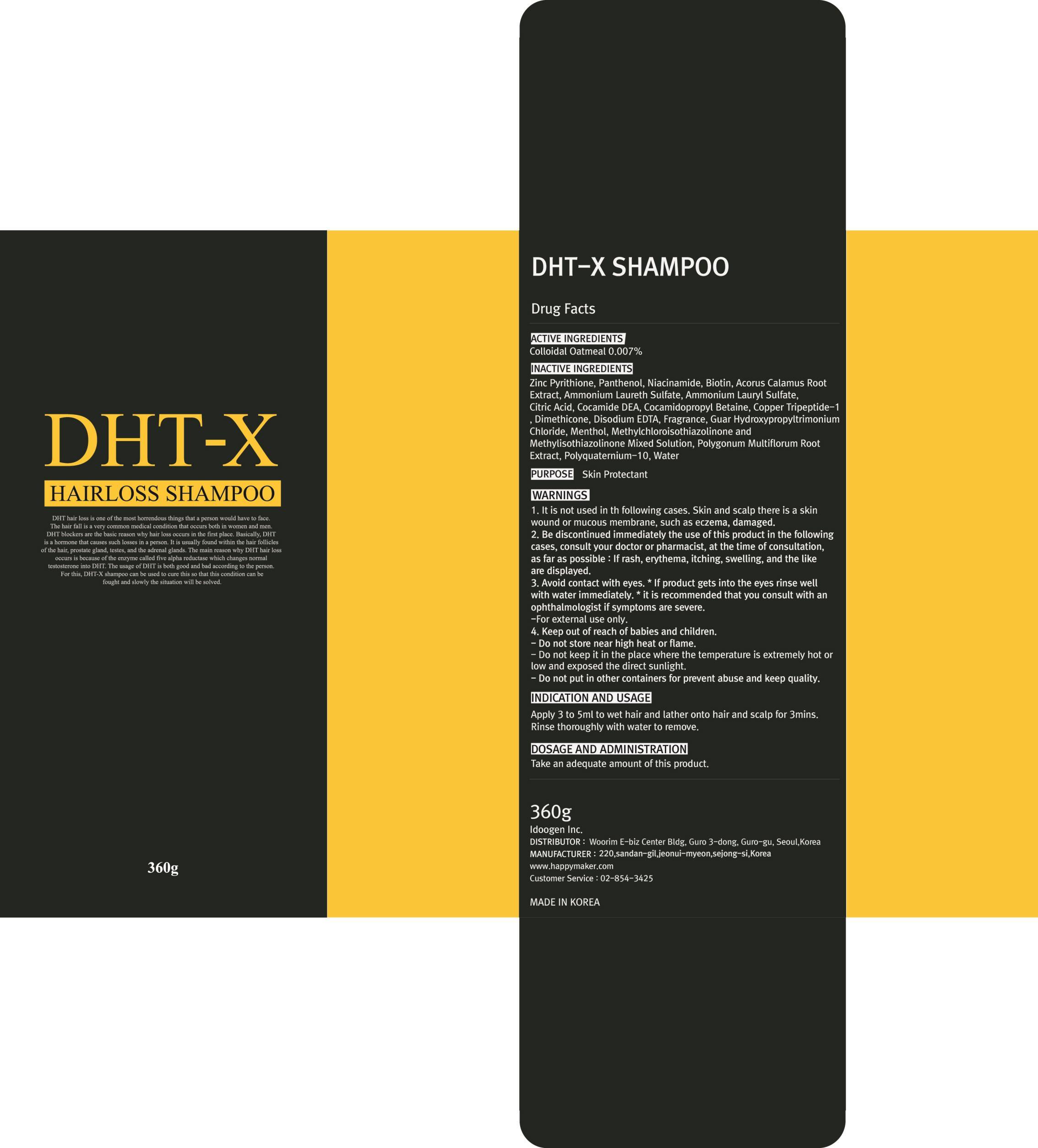 DRUG LABEL: DHT X
NDC: 69281-020 | Form: SHAMPOO
Manufacturer: IDOOGEN CO., LTD.
Category: otc | Type: HUMAN OTC DRUG LABEL
Date: 20141020

ACTIVE INGREDIENTS: OATMEAL 0.025 g/360 g
INACTIVE INGREDIENTS: PYRITHIONE ZINC; Panthenol

ACTIVE INGREDIENT

ACTIVE INGREDIENT: Colloidal Oatmeal 0.007%

INACTIVE INGREDIENT

INACTIVE INGREDIENTS :
Zinc Pyrithione, Panthenol, Niacinamide, Biotin, Acorus Calamus Root Extract, Ammonium Laureth Sulfate, Ammonium Lauryl Sulfate, Citric Acid, Cocamide DEA, Cocamidopropyl Betaine, Copper Tripeptide-1, Dimethicone, Disodium EDTA, Fragrance, Guar Hydroxypropyltrimonium Chloride, Menthol, Methylchloroisothiazolinone and Methylisothiazolinone Mixed Solution, Polygonum Multiflorum Root Extract, Polyquaternium-10, Water

PURPOSE

PURPOSE : Skin Protectant

WARNINGS

1. It is not used in the following cases. Skin and scalp there is a skin wound or mucous membrane, such as eczema, damaged
2. Be discontinued immediately the use of this product in the following cases, consult your doctor or pharmacist, at the time of consultation, as far as possible : If rash, erythema, itching, swelling, and the like are displayed
3. Avoid contact with eyes. * If product gets into the eyes rinse well with water immediately. * it is recommended that you consult with an ophthalmologist if symptoms are severe
- For external use only
4. Keep out of reach of babies and children
- Do not store near high heat or flame
- Do not keep it in the place where the temperature is extremely hot or low and exposed the direct sunlight.
- Do not put in other containers for prevent abuse and keep quality

KEEP OUT OF REACH OF CHILDREN

Keep out of reach of babies and children

INDICATIONS & USAGE

INDICATION AND USAGE :
Apply 3 to 5ml to wet hair and lather onto hair and scalp for 3mins. Rinse thoroughly with water to remove

DOSAGE & ADMINISTRATION

DOSAGE AND ADMINISTRATION :
Take an adequate amount of this product